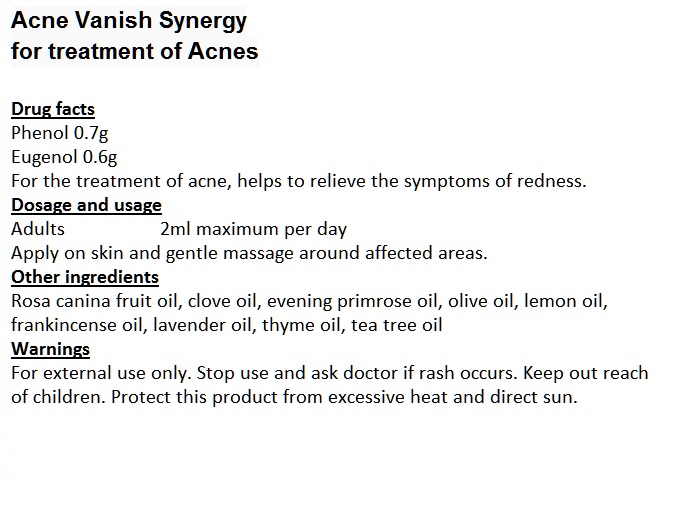 DRUG LABEL: Acne Vanish Synergy
NDC: 70470-1002 | Form: OIL
Manufacturer: PHYTOPIA CO., LTD.
Category: otc | Type: HUMAN OTC DRUG LABEL
Date: 20191231

ACTIVE INGREDIENTS: THYMOL 0.7 g/50 g
INACTIVE INGREDIENTS: TEA TREE OIL; THYME OIL; ROSA CANINA FRUIT OIL; CLOVE OIL; OLIVE OIL; LEMON OIL; FRANKINCENSE OIL; LAVENDER OIL; EVENING PRIMROSE OIL

Drug facts

Phenol 0.7g

Eugenol 0.6g

For the treatment of acne, helps to relieve the symptoms of redness.

DOSAGE AND ADMINISTRATION

Adults 2ml maximum per day

Apply on skin and gentle massage around affected areas.

Directions

Apply on skin and gentle massage around infected area.

INACTIVE INGREDIENT

Other ingredients

Rosa canina fruit oil, clove oil, evening primrose oil, olive oil, lemon oil, frankincense oil, lavender oil, thyme oil, tea tree oil

Warning

- For external use only.
- Stop use and ask doctor if rash occurs.
- Keep out reach of children.

Warning

Keep out reach of children.

Other Information

Protect this product from excessive heat and direct sun.